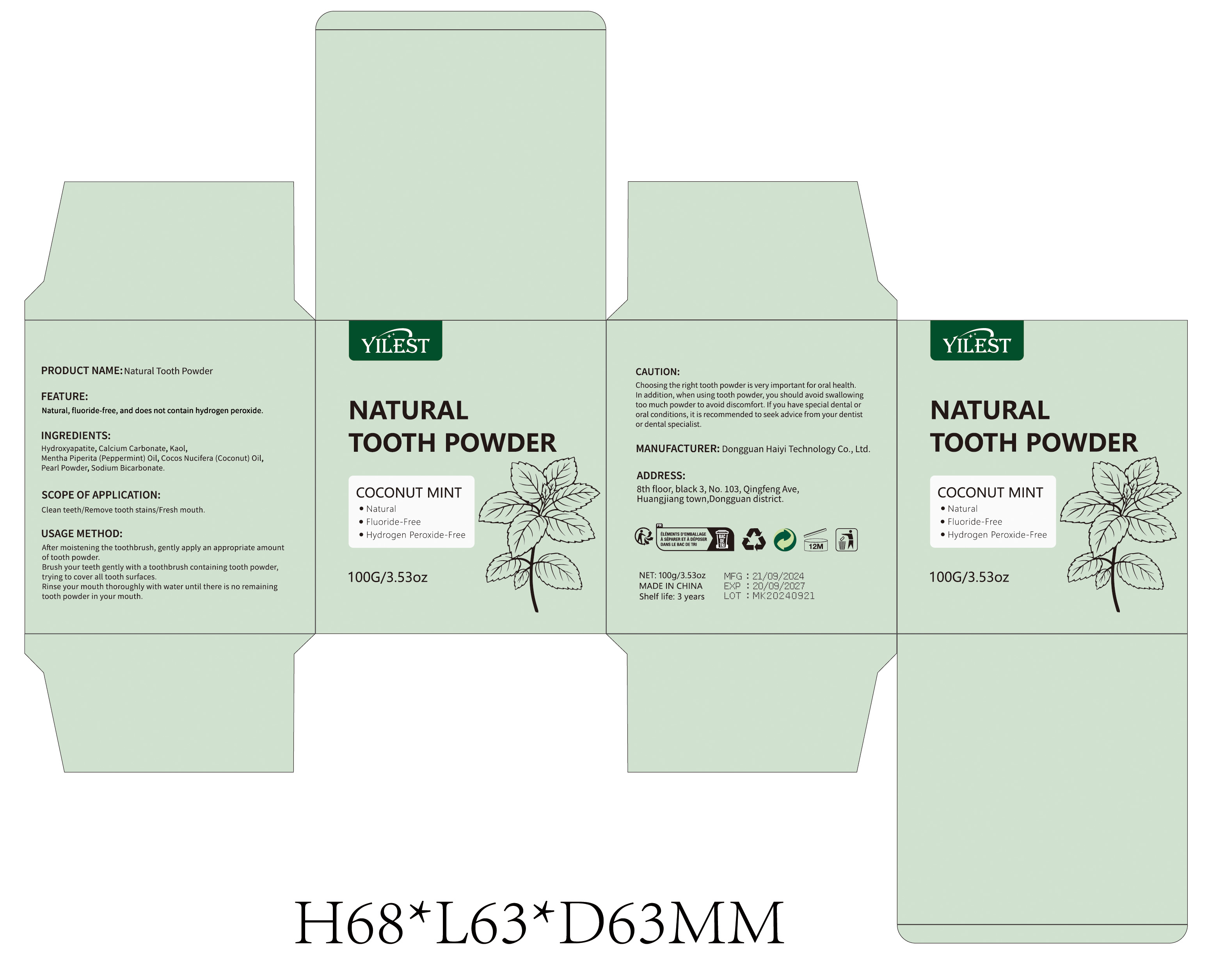 DRUG LABEL: Natural Tooth Powder
NDC: 84732-049 | Form: POWDER
Manufacturer: Dongguan Haiyi Technology Co.,Ltd.
Category: otc | Type: HUMAN OTC DRUG LABEL
Date: 20241016

ACTIVE INGREDIENTS: CALCIUM CARBONATE 5 mg/50 g
INACTIVE INGREDIENTS: KAOLIN; HYDROXYAPATITE/BETA-TRICALCIUM PHOSPHATE (HA/TCP); COCONUT OIL; PEARL (HYRIOPSIS CUMINGII); SODIUM BICARBONATE; PEPPERMINT OIL

Active ingredient

Sodium Bicarbonate

Inactive ingredient

Hydroxyapatite,Calcium Carbonate, Kaol,Mentha Piperita (Peppermint) Oil, Cocos Nucifera (Coconut) Oil,Pearl Powder,

Purpose section

Natural, fluoride-free, and does not contain hydrogen peroxide.

Warning

Choosingthe right tooth powder is very important for oral health.In addition, when using tooth powder, you should avoid swallowing too much powder to avoid discomfort. lf you have special dental ororal conditions, it is recommended to seek advice from your dentistor dental specialist.

stop use

This product may cause allergic reactions in asmall number of people.
lf you experience any discomfort,please stop using it immediately.

not use

Not suitable for use by children, pregnantor breast feeding people.

OUT OF CHILDREN

KEEP THE PRODUCT OUT OF REACH OF CHILDREN to

HOW TO USE

After moistening the toothbrush, gently apply an appropriate amountof tooth powder.Brush your teeth gently with a toothbrush containing tooth powder,trying to cover all tooth surfaces.Rinse your mouth thoroughly with water until there is no remainingtooth powder in your mouth.

DOSAGE

Once a day in the morning and evening